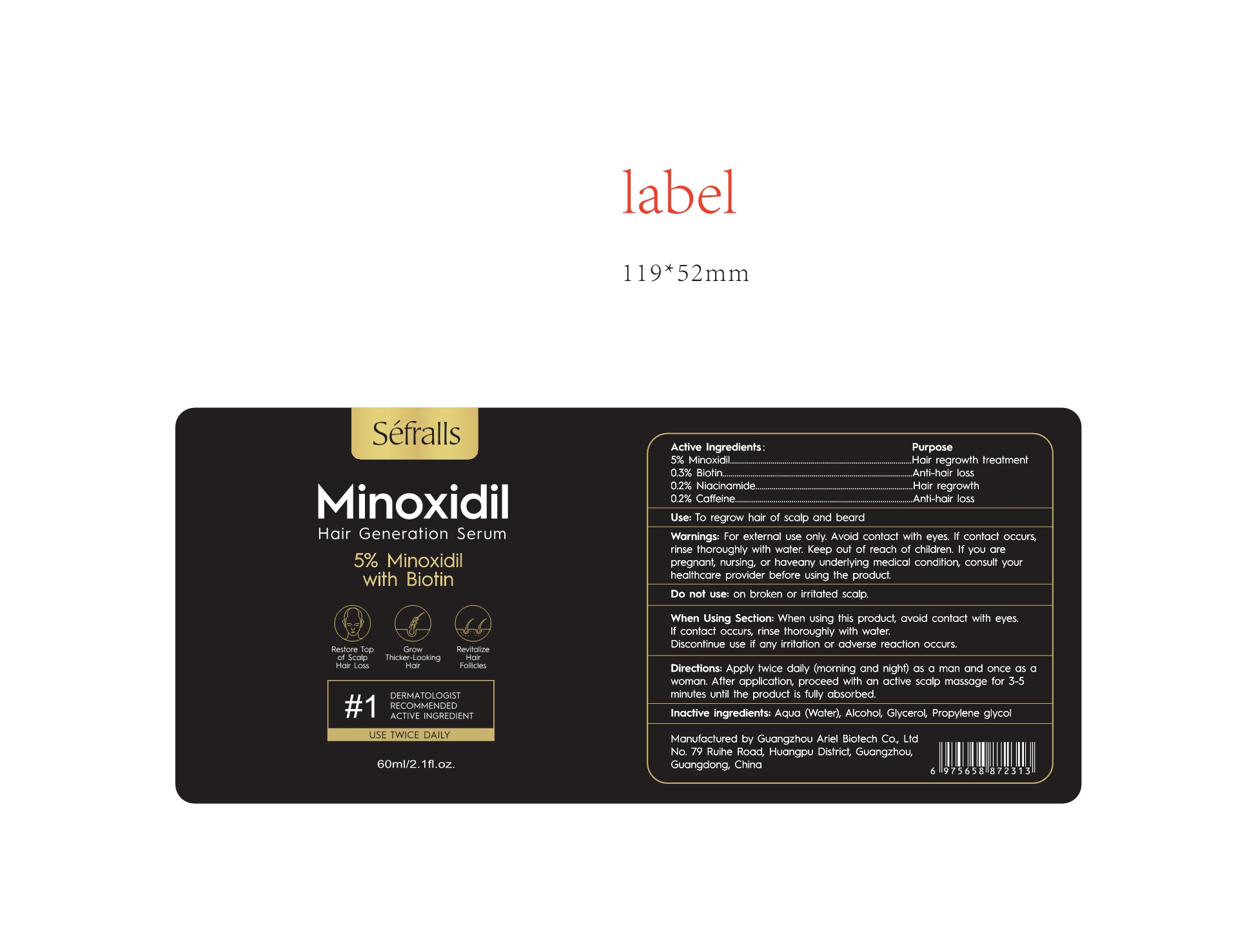 DRUG LABEL: 5% Minoxidil Hair Growth Serum
NDC: 84148-001 | Form: LIQUID
Manufacturer: Guangzhou Ariel Biotech Co., Ltd.
Category: otc | Type: HUMAN OTC DRUG LABEL
Date: 20240312

ACTIVE INGREDIENTS: NIACINAMIDE 0.2 g/100 g; MINOXIDIL 5 g/100 g; CAFFEINE 0.2 g/100 g; BIOTIN 0.3 g/100 g
INACTIVE INGREDIENTS: GLYCERIN; DIPROPYLENE GLYCOL; WATER; ALCOHOL

ACTIVE INGREDIENT

5% Minoxidil.........Hair regrowth treatment

0.3% Biotin...........Anti-hair loss

0.2% Niacinamide.......Hair regrowth

0.2% Caffeine.......Anti-hair loss

Use:

To regrow hair of scalp and beard

Warnings:

For external use only. Avoid contact with eyes. lf contact occurs, rinse thoroughly with water. Keep out of reach of children.If you are pregnant, nursing, or haveany underlying medical condition, consult your healthcare provider before using the product.

WHEN USING SECTION:

When using this product, avoid contact with eyes. lf contact occurs, rinse thoroughly with water.

Discontinue use if any irritation or adverse reaction occurs.

Directions

Apply twice daily(morning and night) as a man and once as a woman. After application, proceed with an active scalp massage for 3-5 minutes until the product is fully absorbed

Inactive ingredients:

Aqua(Water),Alcohol ,Glycerol,Propylene glycol

OTHER SAFETY INFORMATION

Manufactured by Guangzhou Ariel Biotech Co., Ltd

No. 79 Ruihe Road, Huangpu District, Guangzhou,Guangdong, China

DOSAGE&ADMINISTRATION SECTION

PURPOSE

5% Minoxidil.........Hair regrowth treatment

0.3% Biotin...........Anti-hair loss

0.2% Niacinamide.......Hair regrowth

0.2% Caffeine.......Anti-hair loss

Keep out of reach of children.

INDICATIONS AND USAGE

To regrow hair of scalp and beard